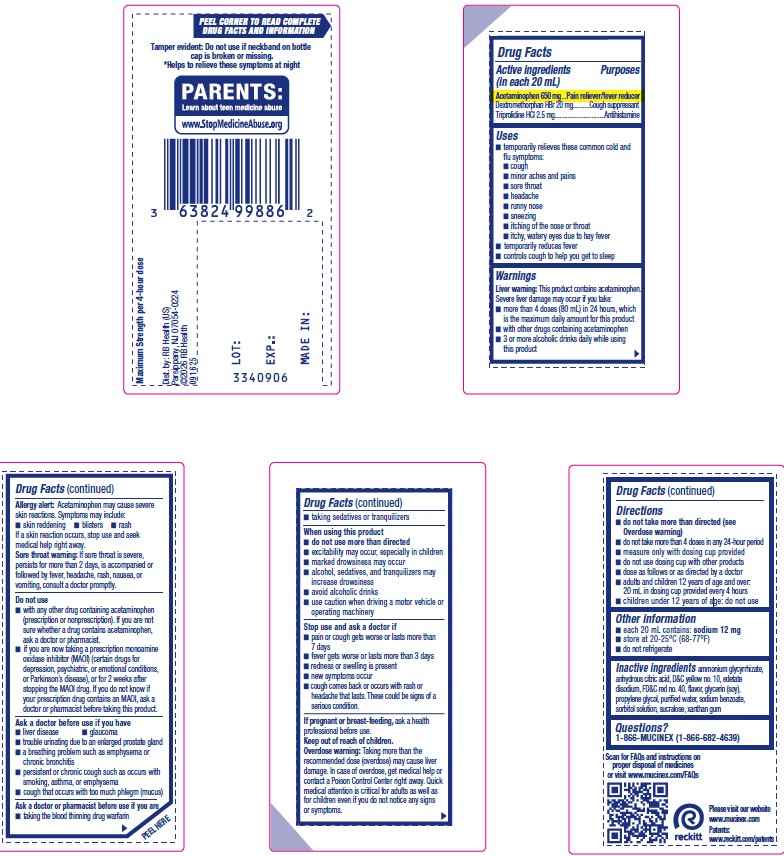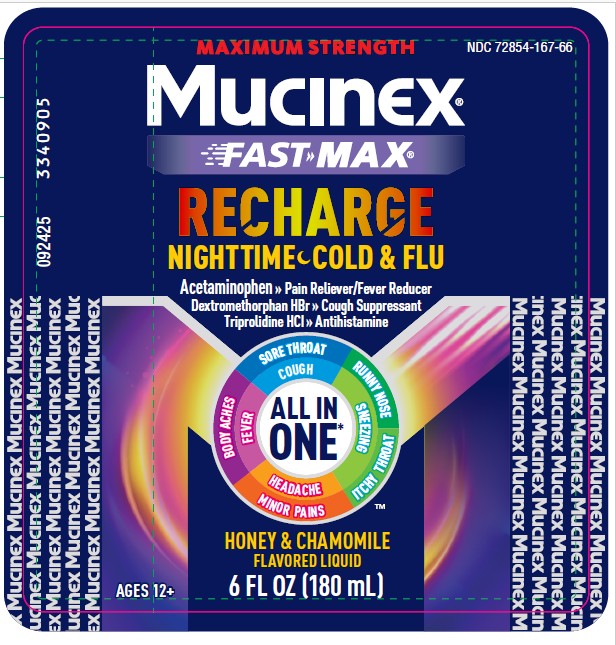 DRUG LABEL: Mucinex Fast-Max Recharge Nighttime Cold and Flu
NDC: 72854-167 | Form: SOLUTION
Manufacturer: RB Health (US) LLC
Category: otc | Type: HUMAN OTC DRUG LABEL
Date: 20260225

ACTIVE INGREDIENTS: ACETAMINOPHEN 650 mg/20 mL; DEXTROMETHORPHAN HYDROBROMIDE 20 mg/20 mL; TRIPROLIDINE HYDROCHLORIDE 2.5 mg/20 mL
INACTIVE INGREDIENTS: GLYCERIN; AMMONIUM GLYCYRRHIZATE; ANHYDROUS CITRIC ACID; EDETATE DISODIUM; D&C YELLOW NO. 10; FD&C RED NO. 40; PROPYLENE GLYCOL; SODIUM BENZOATE; SORBITOL; SUCRALOSE; WATER; XANTHAN GUM

Mucinex® Nightshift
Cold and Flu

Drug Facts

ACTIVE INGREDIENT

PURPOSE

Active ingredients (in each 20 mL) | Purposes
Acetaminophen 650 mg | Pain reliever/fever reducer
Dextromethorphan HBr 20 mg | Cough suppressant
Triprolidine HCl 2.5 mg | Antihistamine

Uses

- temporarily relieves these common cold and flu symptoms:
  - cough
  - minor aches and pains
  - sore throat
  - headache
  - runny nose
  - sneezing
  - itching of the nose or throat
  - itchy, watery eyes due to hay fever
- temporarily reduces fever
- controls cough to help you get to sleep

Warnings Section:

Liver warning

This product contains acetaminophen. Severe liver damage may occur if you take:

- more than 4 doses (80 mL) in 24 hours,, which is the maximum daily amount
- with other drugs containing acetaminophen
- 3 or more alcoholic drinks daily while using this product

Allergy alert

Acetaminophen may cause severe skin reactions. Symptoms may include:

- skin reddening
- blisters
- rash

If a skin reaction occurs, stop use and seek medical help right away.

Sore throat warning

If sore throat is severe, persists for more than 2 days, is accompanied or followed by fever, headache, rash, nausea, or vomiting, consult a doctor promptly.

Do not use

- with any other drug containing acetaminophen (prescription or nonprescription). If you are not sure whether a drug contains acetaminophen, ask a doctor or pharmacist.
- if you are now taking a prescription monoamine oxidase inhibitor (MAOI) (certain drugs for depression, psychiatric, or emotional conditions, or Parkinson's disease), or for 2 weeks after stopping the MAOI drug. If you do not know if your prescription drug contains an MAOI, ask a doctor or pharmacist before taking this product.

Ask a doctor before use if you have

- liver disease
- glaucoma
- trouble urinating due to an enlarged prostate gland
- a breathing problem such as emphysema or chronic bronchitis
- persistent or chronic cough such as occurs with smoking, asthma, or emphysema
- cough that occurs with too much phlegm (mucus)

Ask a doctor or pharmacist before use if you are

- taking the blood thinning drug warfarin
- taking sedatives or tranquilizers

When using this product

- do not use more than directed
- excitability may occur, especially in children
- marked drowsiness may occur
- alcohol, sedatives, and tranquilizers may increase drowsiness
- avoid alcoholic drinks
- use caution when driving a motor vehicle or operating machinery

Stop use and ask a doctor if

- pain or cough gets worse or lasts more than 7 days
- fever gets worse or lasts more than 3 days
- redness or swelling is present
- new symptoms occur
- cough comes back, or occurs with fever, rash, or headache that lasts. These could be signs of a serious condition.

PREGNANCY OR BREAST FEEDING

If pregnant or breast-feeding,ask a health professional before use.

Keep out of reach of children.

Overdose warning

Taking more than the recommended dose (overdose) may cause liver damage. In case of overdose, get medical help or contact a Poison Control Center right away. Quick medical attention is critical for adults as well as for children even if you do not notice any signs or symptoms.

Directions

- do not take more than directed (see Overdose warning)
- do not take more than 4 doses in any 24-hour period
- measure only with dosing cup provided
- do not use dosing cup with other products
- dose as follows or as directed by a doctor
- adults and children 12 years of age and older: 20 mL in dosing cup provided every 4 hours
- children under 12 years of age: do not use

Other information

- each 20 mL contains: sodium 12 mg
- store at 20-25°C (68-77°F)
- do not refrigerate

Inactive ingredients

ammonium glycyrrhizate,
anhydrous citric acid, D&C yellow no. 10, edetate
disodium, FD&C red no. 40, flavor, glycerin (soy),
propylene glycol, purified water, sodium benzoate,
sorbitol solution, sucralose, xanthan gum

Questions?

1-866-MUCINEX (1-866-682-4639)

Dist. by: RB Health (US)
Parsippany, NJ 07054-0224

PRINCIPAL DISPLAY PANEL - 180 mL Bottle Label

NDC 72854-167-66

Mucinex®

Acetaminophen – Pain Reliever/Fever Reducer
Dextromethorphan HBr – Cough Suppressant
Triprolidine HCl – Antihistamine

6 FL OZ (180 mL)
FOR AGES 12+